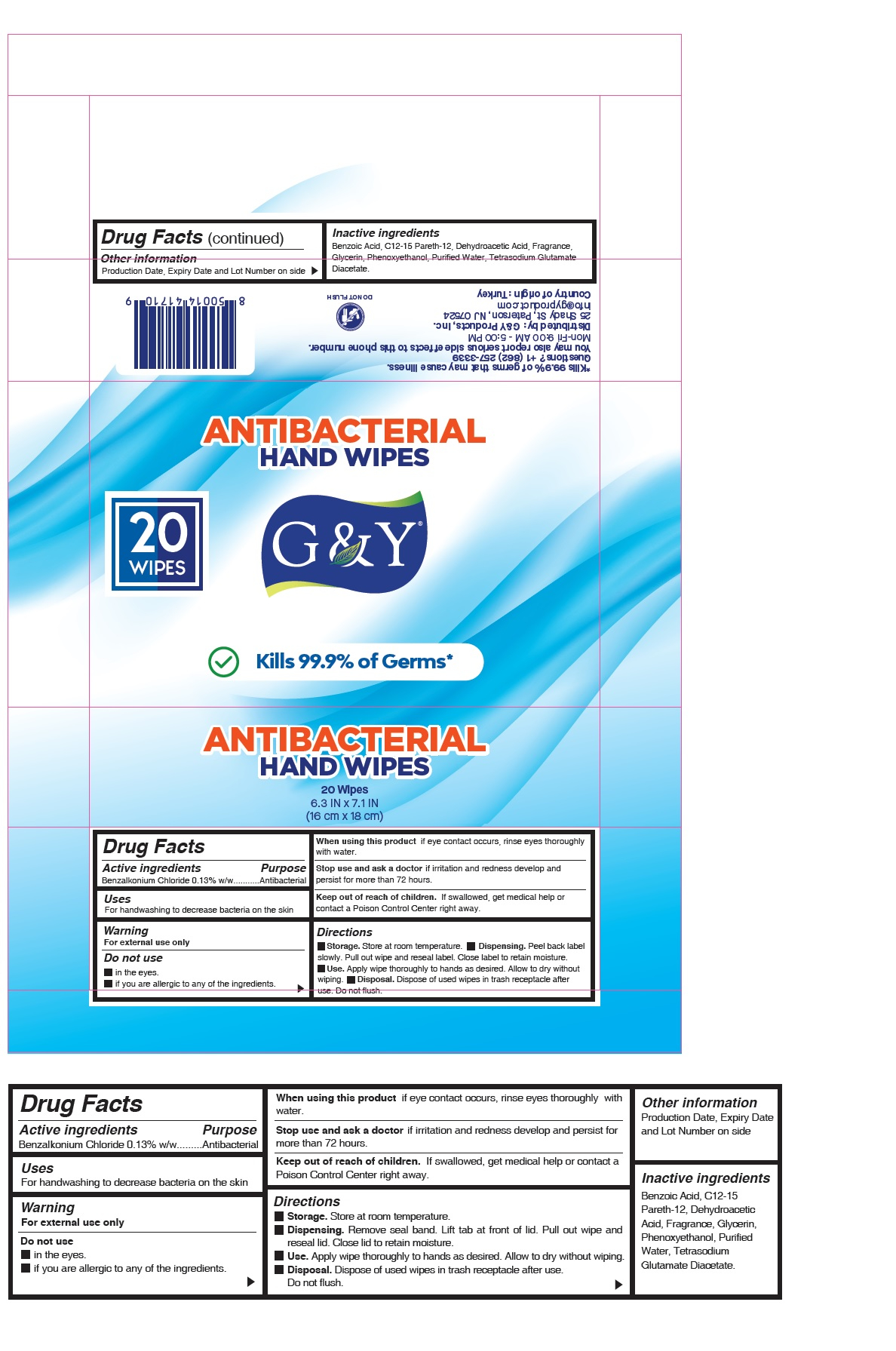 DRUG LABEL: G AND Y ANTIBACTERIAL WET WIPES
NDC: 80903-013 | Form: CLOTH
Manufacturer: G&Y PRODUCTS INC.
Category: otc | Type: HUMAN OTC DRUG LABEL
Date: 20220201

ACTIVE INGREDIENTS: BENZALKONIUM CHLORIDE 0.13 g/3.5 mL
INACTIVE INGREDIENTS: WATER; DEHYDROACETIC ACID; PHENOXYETHANOL; TETRASODIUM GLUTAMATE DIACETATE; C12-15 PARETH-12; GLYCERIN; BENZOIC ACID

Active Ingredient(s)

Benzalkonium Chloride 0.13% w/w

Purpose

Antibacterial

Uses

For handwashing to decrease bacteria on the skin.

Warnings

For external use only.

Do not use

- in the eyes.
- if you are allergic to any of the ingredients.

When using this product

if eye contact occurs, rinse eyes thoroughly with water.

Stop use and ask a doctor

if irritation and redness develop and persist for more than 72 hours.

Keep out of reach of children

if swallowed, get medical help or contact a Poison Control Center right away.

Directions

- Storage: Store at room temperature
- Dispensing: Peel back label slowly. Pull out wipe and reseal label. Close label to retain moisture.
- Use: Apply wipe thoroughly to hands as desired. Allow to dry without wiping.
- Disposal: Dispose of used wipes in trash receptable after use. Do not flush.

Inactive Ingredients

Benzoic Acid, C12-15 Pareth-12, Dehydroacetic Acid, Fragrance, Glycerin, Phenoxyethanol, Purified Water, Tetrasodium Glutamate Diacetate.

Package label

Kills 99.9% of Germs that may cause illness.

6.3 IN x 7.1 IN

(16 cm x 18 cm)

Questions? +1 (862) 257-3339

You may also report serious side effects to this phone number.

Mon-Fri 9:00 AM - 5:00 PM

Distributed by: G&Y Products, Inc.

25 Shady St, Paterson, NJ 07524

info@gyproduct.com

Country of origin: Turkey